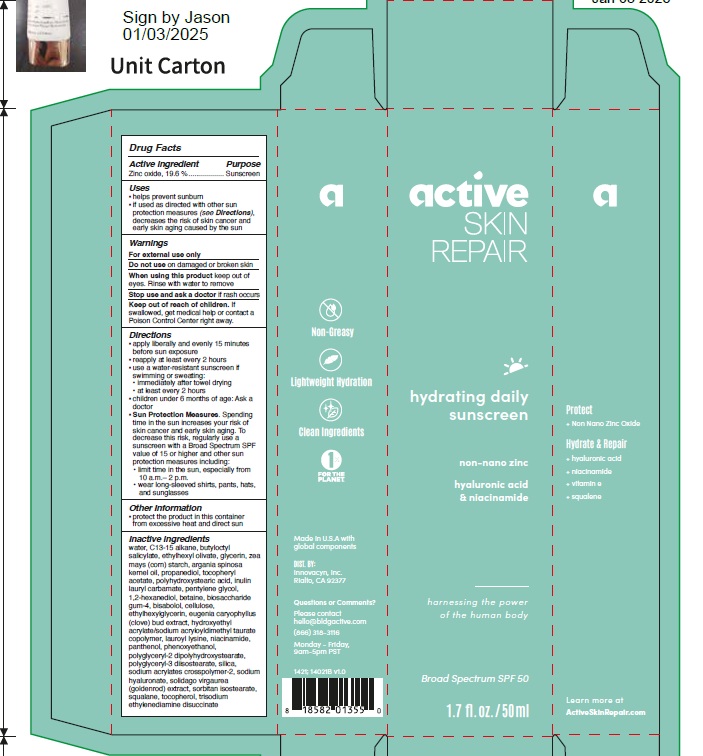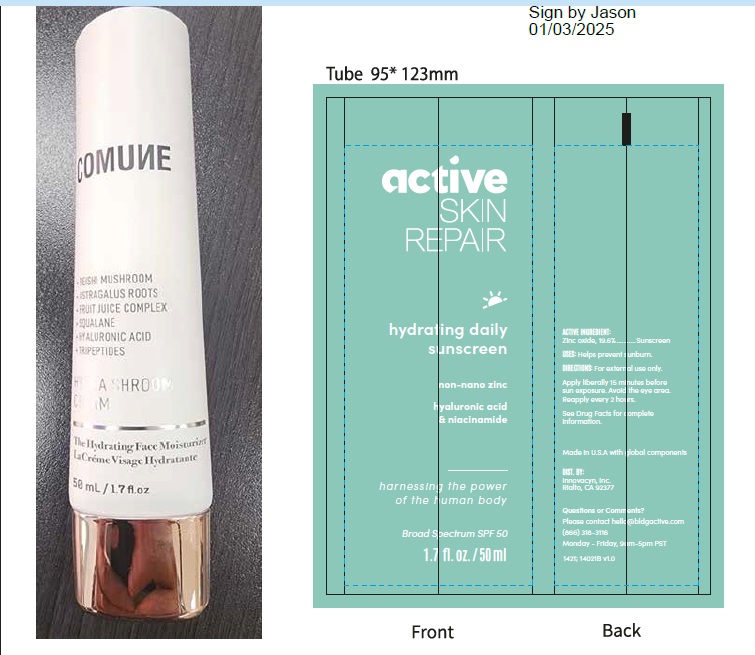 DRUG LABEL: Active Skin Repair hydrating daily sunscreen
NDC: 70489-1615 | Form: LOTION
Manufacturer: Innovacyn, Inc.
Category: otc | Type: HUMAN OTC DRUG LABEL
Date: 20250626

ACTIVE INGREDIENTS: ZINC OXIDE 19.6 g/100 mL
INACTIVE INGREDIENTS: WATER; C13-15 ALKANE; BUTYLOCTYL SALICYLATE; ETHYLHEXYL OLIVATE; GLYCERIN; ZEA MAYS (CORN) STARCH; ARGANIA SPINOSA KERNEL OIL; PROPANEDIOL; .ALPHA.-TOCOPHEROL ACETATE; POLYHYDROXYSTEARIC ACID (2300 MW); INULIN LAURYL CARBAMATE; PENTYLENE GLYCOL; HYDROXYETHYL ACRYLATE/SODIUM ACRYLOYLDIMETHYL TAURATE COPOLYMER (100000 MPA.S AT 1.5%); PHENOXYETHANOL; SODIUM ACRYLATES CROSSPOLYMER-2; BISABOLOL; LAUROYL LYSINE; CLOVE; SQUALANE; SOLIDAGO VIRGAUREA FLOWERING TOP; TOCOPHEROL; BETAINE; NIACINAMIDE; PANTHENOL; POLYGLYCERYL-2 DIPOLYHYDROXYSTEARATE; POLYGLYCERYL-3 DIISOSTEARATE; POWDERED CELLULOSE; ETHYLHEXYLGLYCERIN; 1,2-HEXANEDIOL; SORBITAN ISOSTEARATE; TRISODIUM ETHYLENEDIAMINE DISUCCINATE; BIOSACCHARIDE GUM-4; SILICON DIOXIDE; HYALURONATE SODIUM

Active ingredient

Zinc oxide, 19.6 %

Purpose

Sunscreen

Uses

- helps prevent sunburn
- if used as directed with other sun protection measures (see Directions), decreases the risk of skin cancer and early skin aging caused by the sun

Warnings

For external use only
Do not useon damaged or broken skin
When using this productkeep out of eyes. Rinse with water to remove
Stop use and ask a doctor ifrash occurs
Keep out of reach of children. If swallowed, get medical help or contact a Poison Control Center right away.

Directions

- apply liberally and evenly 15 minutes before sun exposure
- reapply at least every 2 hours
- use a water-resistant sunscreen if swimming or sweating:
- immediately after towel drying
- at least every 2 hours
- children under 6 months of age: Ask a doctor
- Sun Protection Measures. Spending time in the sun increases your risk of skin cancer and early skin aging. To decrease this risk, regularly use a sunscreen with a Broad Spectrum SPF value of 15 or higher and other sun protection measures including:

• limit time in the sun, especially from 10 a.m.– 2 p.m.
• wear long-sleeved shirts, pants, hats, and sunglasses

Other Information

- protect the product in this container from excessive heat and direct sun

Inactive ingredients

water, C13-15 alkane, butyloctyl salicylate, ethylhexyl olivate, glycerin, zea mays (corn) starch, argania spinosa kernel oil, propanediol, tocopheryl acetate, polyhydroxystearic acid, inulin lauryl carbamate, pentylene glycol, 1,2-hexanediol, betaine, biosaccharide gum-4, bisabolol, cellulose, ethylhexylglycerin, eugenia caryophyllus (clove) bud extract, hydroxyethyl acrylate/sodium acryloyldimethyl taurate copolymer, lauroyl lysine, niacinamide, panthenol, phenoxyethanol, polyglyceryl-2 dipolyhydroxystearate, polyglyceryl-3 diisostearate, silica, sodium acrylates crosspolymer-2, sodium hyaluronate, solidago virgaurea (goldenrod) extract, sorbitan isostearate, squalane, tocopherol, trisodium ethylenediamine disuccinate